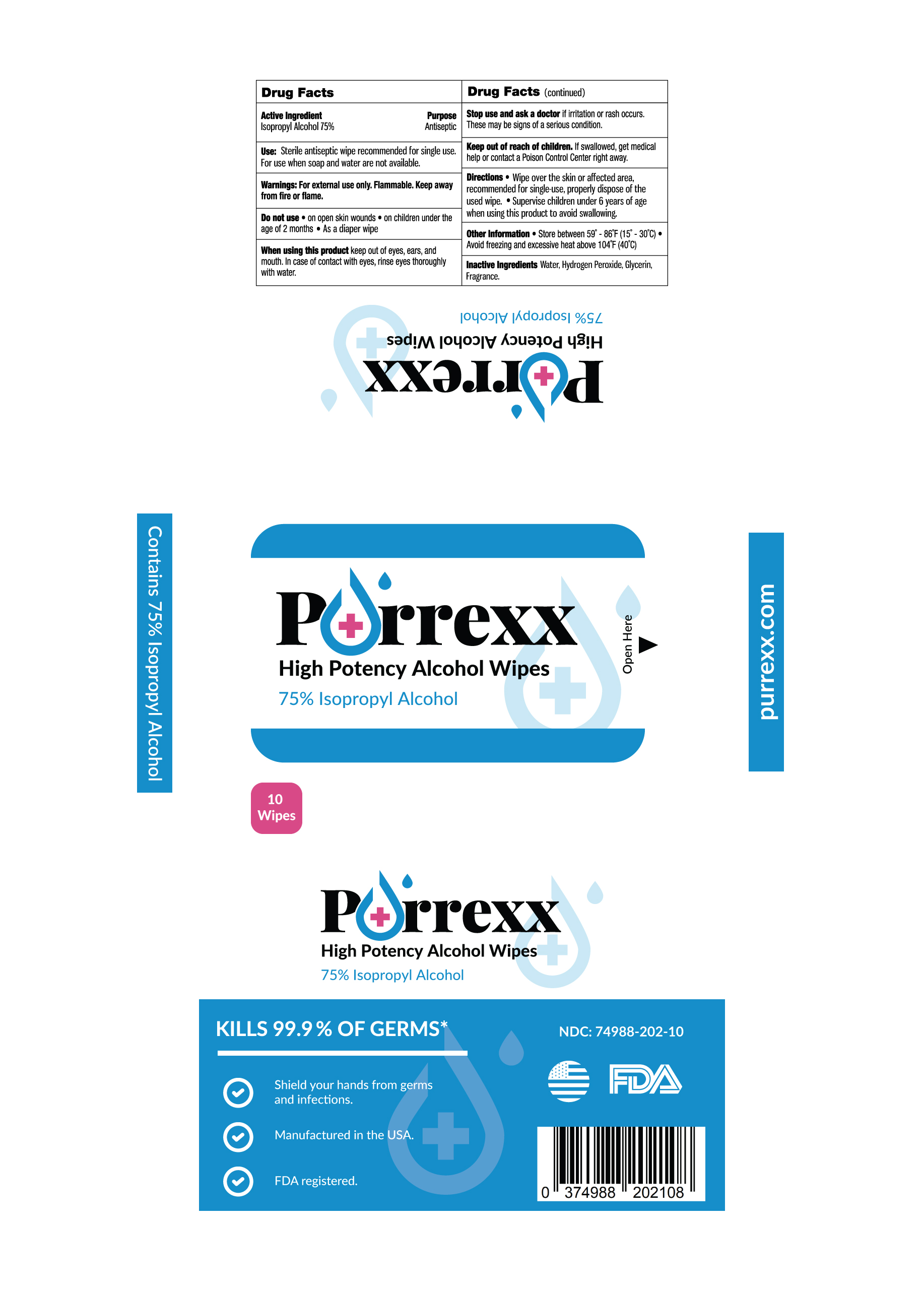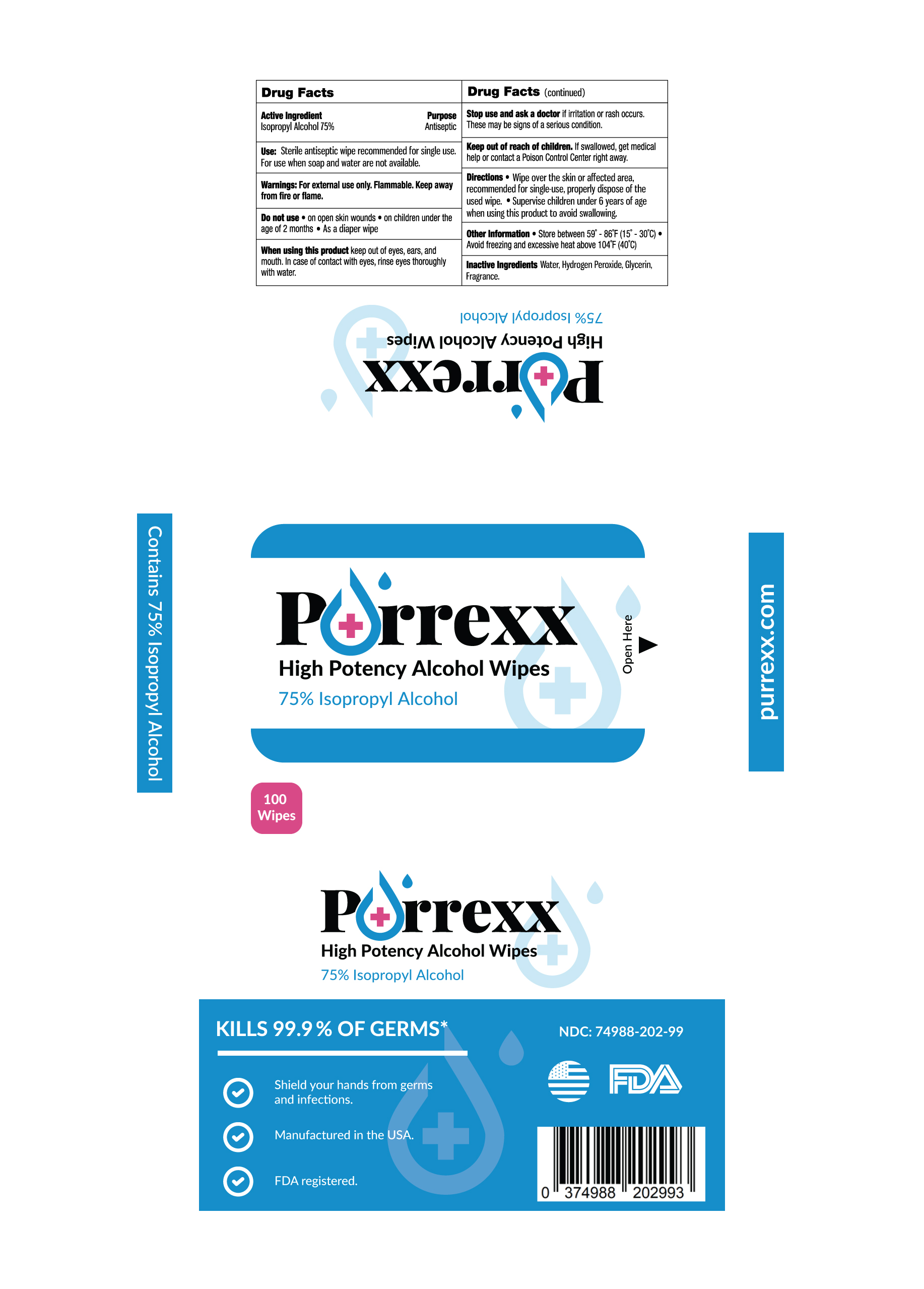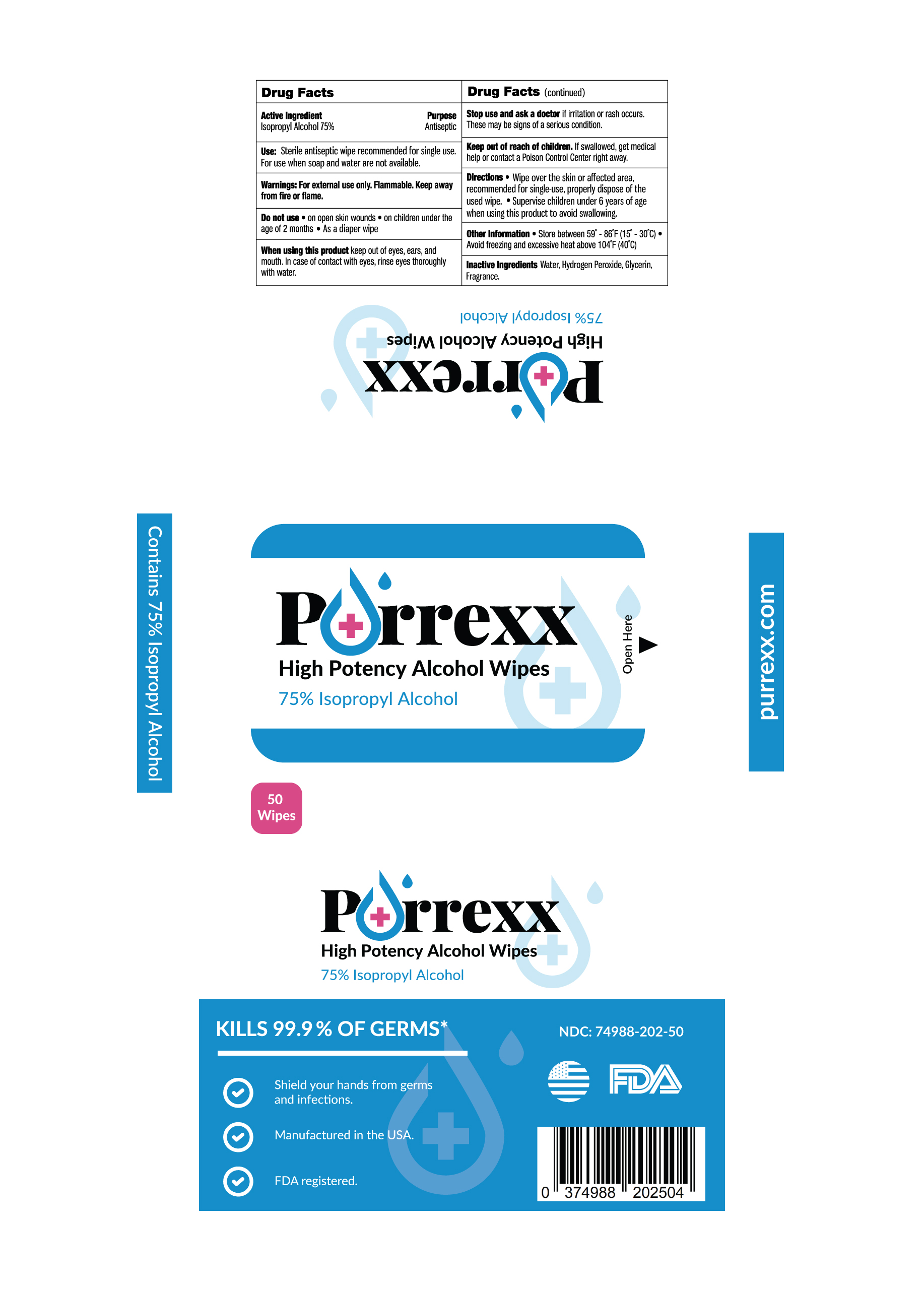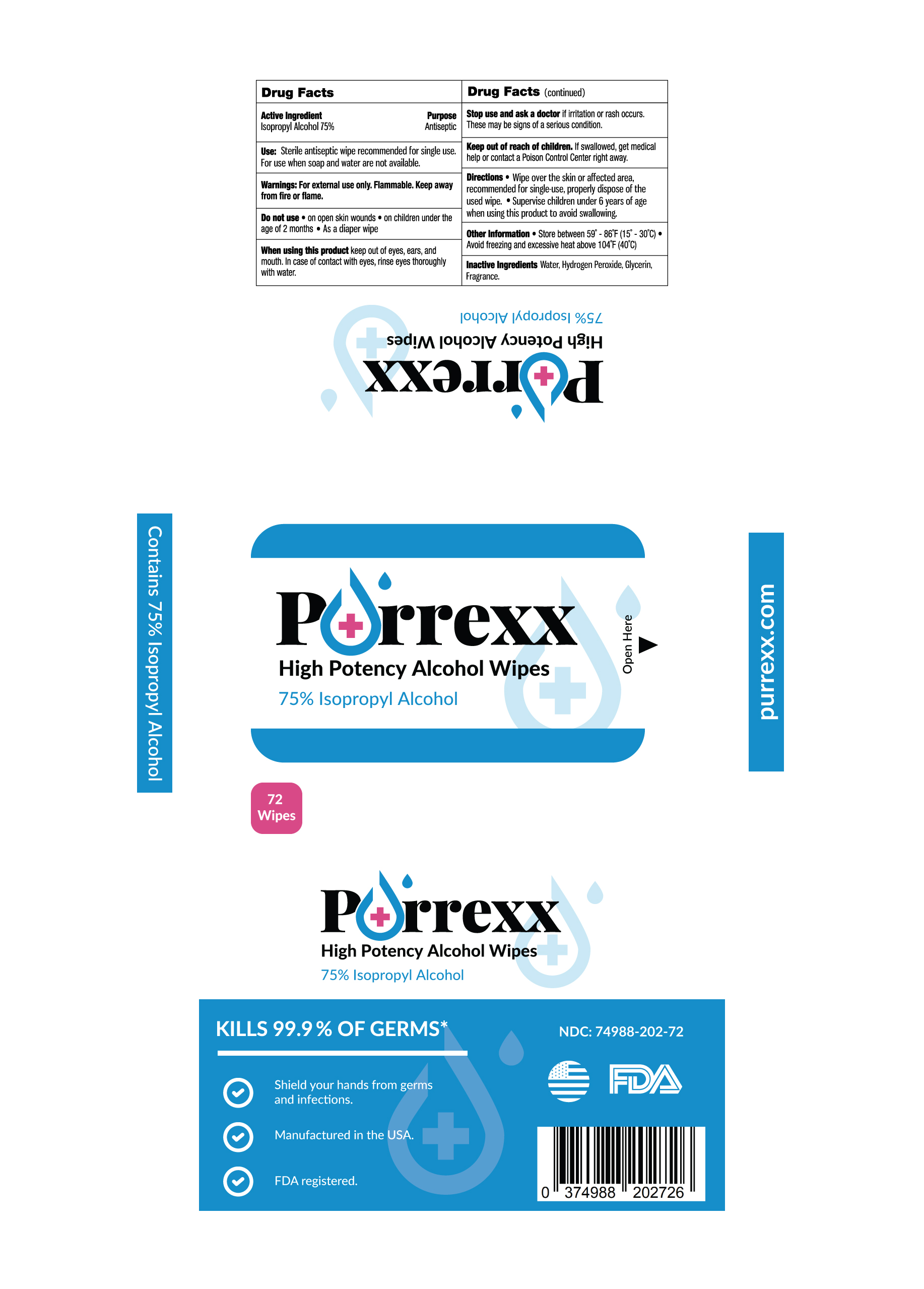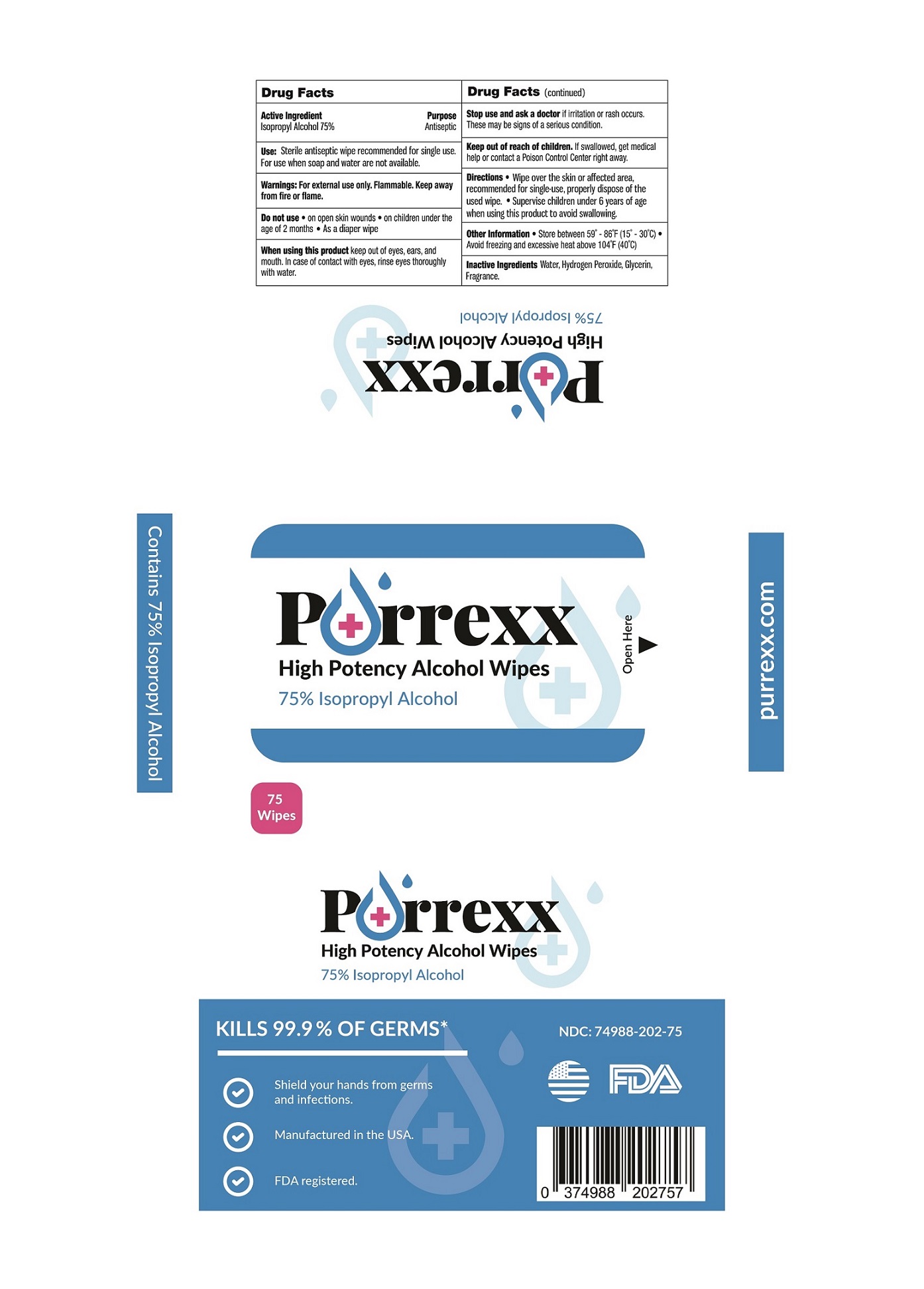 DRUG LABEL: PUREXX IPA Wipes
NDC: 74988-202 | Form: CLOTH
Manufacturer: SanitizeNow Inc.
Category: otc | Type: HUMAN OTC DRUG LABEL
Date: 20210129

ACTIVE INGREDIENTS: ISOPROPYL ALCOHOL 75 mL/100 1
INACTIVE INGREDIENTS: GLYCERIN; HYDROGEN PEROXIDE; WATER

Disclaimer: Most OTC drugs are not reviewed and approved by FDA; however, they may be marketed if they comply with applicable regulations and policies. FDA has not evaluated whether this product complies.

Active Ingredient(s)

Isopropyl Alcohol 75% v/v. Purpose: Antiseptic

Purpose

Antiseptic

Use

Sterile antiseptic wipe recommended for single use.

For use when soap and water are not available.

Warnings

For external use only. Flammable. Keep away from heat or flame

Do not use

- In children less than 2 months of age
- As a diaper wipe
- On open skin wounds
- In eyes. In case of contact, rinse eyes thoroughly with water

When using this product keep out of eyes, ears, and mouth. In case of contact with eyes, rinse eyes thoroughly with water.
Stop use and ask a doctor if irritation or rash occurs. These may be signs of a serious condition.
Keep out of reach of children. If swallowed, get medical help or contact a Poison Control Center right away.

Stop use and ask a doctor if irritation or rash occurs. These may be signs of a serious condition.

Keep out of reach of children. If swallowed, get medical help or contact a Poison Control Center right away.

Directions

- Wipe over the skin or affected area, recommended for single-use, properly dispose of the used wipe.

Other information

- Store between 15-30C (59-86F)
- Avoid freezing and excessive heat above 40C (104F)

Inactive ingredients

Water, Hydrogen Peroxide, Glycerin, Fragrance.

Package Label - Principal Display Panel

10 in 1 PACKET NDC: 74988-202-10

50 in 1 PACKET NDC: 74988-202-50

72 in 1 PACKET NDC: 74988-202-72

100 in 1 PACKET NDC: 74988-202-99

75 in 1 CANISTER NDC: 74988-202-75